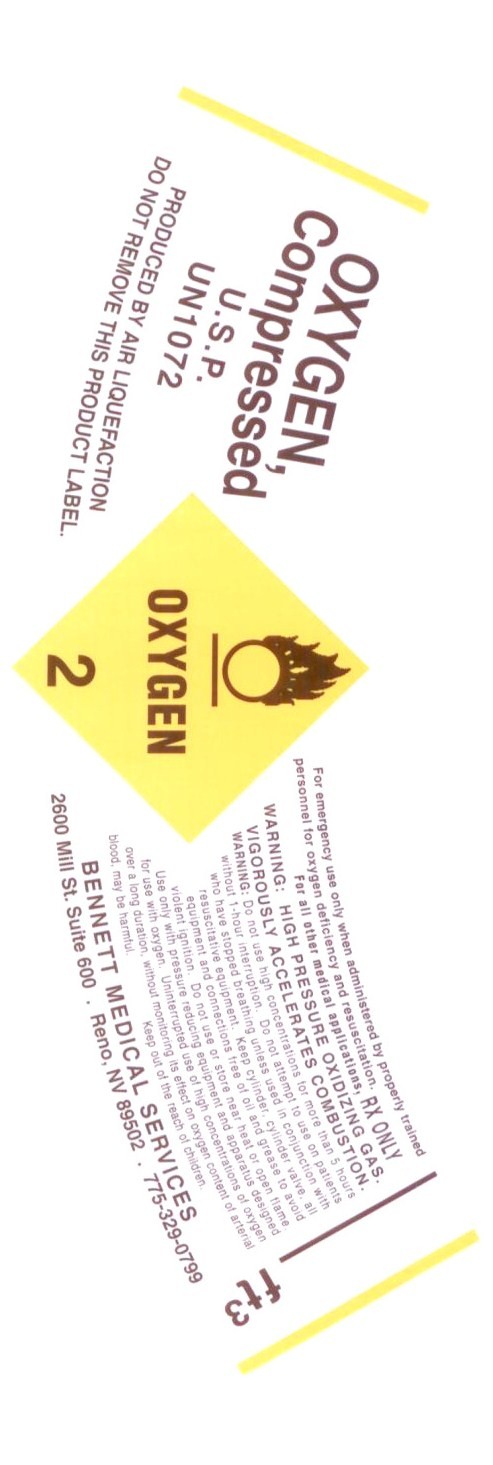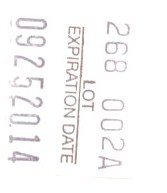 DRUG LABEL: Oxygen
NDC: 61811-0001 | Form: GAS
Manufacturer: Bennett Medical Services
Category: prescription | Type: HUMAN PRESCRIPTION DRUG LABEL
Date: 20091030

ACTIVE INGREDIENTS: Oxygen 99 L/100 L

Oxygen